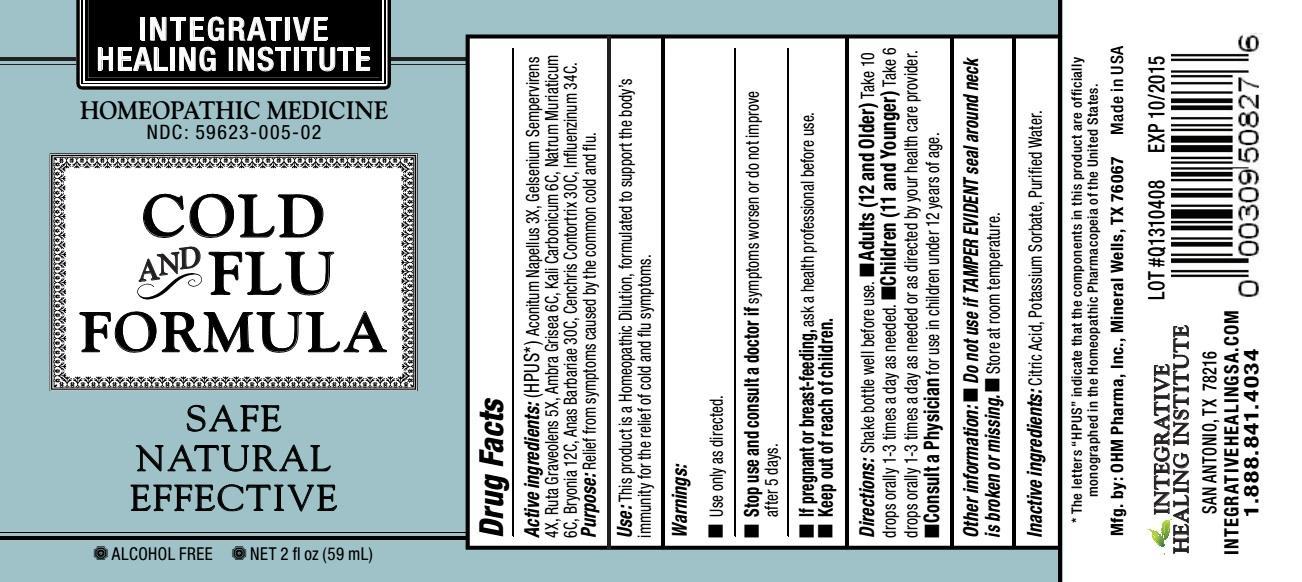 DRUG LABEL: Cold and Flu Formula
                
NDC: 59623-005 | Form: LIQUID
Manufacturer: Integrative Healing Institute, LLC
Category: homeopathic | Type: HUMAN OTC DRUG LABEL
Date: 20190905

ACTIVE INGREDIENTS: ACONITUM NAPELLUS 3 [hp_X]/1 mL; GELSEMIUM SEMPERVIRENS ROOT 4 [hp_X]/1 mL; RUTA GRAVEOLENS FLOWERING TOP     5 [hp_X]/1 mL; AMBERGRIS 6 [hp_C]/1 mL; POTASSIUM CARBONATE     6 [hp_C]/1 mL; SODIUM CHLORIDE 6 [hp_C]/1 mL; BRYONIA ALBA ROOT 12 [hp_C]/1 mL; CAIRINA MOSCHATA HEART/LIVER AUTOLYSATE     30 [hp_C]/1 mL; AGKISTRODON CONTORTRIX VENOM 30 [hp_C]/1 mL; INFLUENZA A VIRUS     34 [hp_C]/1 mL; INFLUENZA B VIRUS     34 [hp_C]/1 mL
INACTIVE INGREDIENTS: WATER; POTASSIUM SORBATE; CITRIC ACID MONOHYDRATE

COLD AND FLU FORMULA

ACTIVE INGREDIENT

Active ingredients (HPUS*): Aconitum Napellus 3X, Gelsemium Sempervirens 4X, Ruta Graveolens 5X, Ambra Grisea 6C, Kali Carbonicum 6C, Natrum Muriaticum 6C, Bryonia 12C, Anas Barbariae 30C, Cenchris Contortrix 30C, Influenzinum 34C.

OTHER SAFETY INFORMATION

* The letters "HPUS" indicate that the components in this product are officially monographed in the Homeopathic Pharmacopeia of the United States.

PURPOSE

Purpose: Relief from symptoms caused by the common cold and flu.

INDICATIONS AND USAGE

Use:This product is a Homeopathic Dilution, formulated to support the body's immunity for the relief of cold and flu symptoms.

Warnings:

- Use only as directed.
- Stop use and consult a doctor if symptoms worsen or do not improve after 5 days.
- If pregnant or breast-feeding, ask a health professional before use.

- Keep out of the reach of children.

DOSAGE AND ADMINISTRATION

Directions: Shake bottle well before use.

- Adults (12 and Older) Take 10 drops orally 1-3 times a day as needed.
- Children (11 and Younger) Take 6 drops orally 1-3 times a day as needed or as directed by your health care provider.
- Consult a Physician for use in children under 12 years of age.

Other information:

- Do not use if TAMPER EVIDENT seal around neck is broken or missing.
- Store at room temperature.

Inactive ingredients: Citric Acid, Potassium Sorbate, Purified Water.

OTHER SAFETY INFORMATION

Mfg. by: OHM Pharma, Inc., Mineral Wells, TX 76067

Made in USA

QUESTIONS

INTEGRATIVE HEALING INSTITUTE

San Antonio, TX 78216

INTEGRATIVEHEALINGSA.COM

1.888.841.4034

PACKAGE LABEL

INTEGRATIVE HEALING INSTITUTE

HOMEOPATHIC MEDICINE

NDC: 59623-005-02

COLD AND FLU FORMULA

SAFE

NATURAL

EFFECTIVE

ALCOHOL FREE

NET 2 fl oz (59mL)